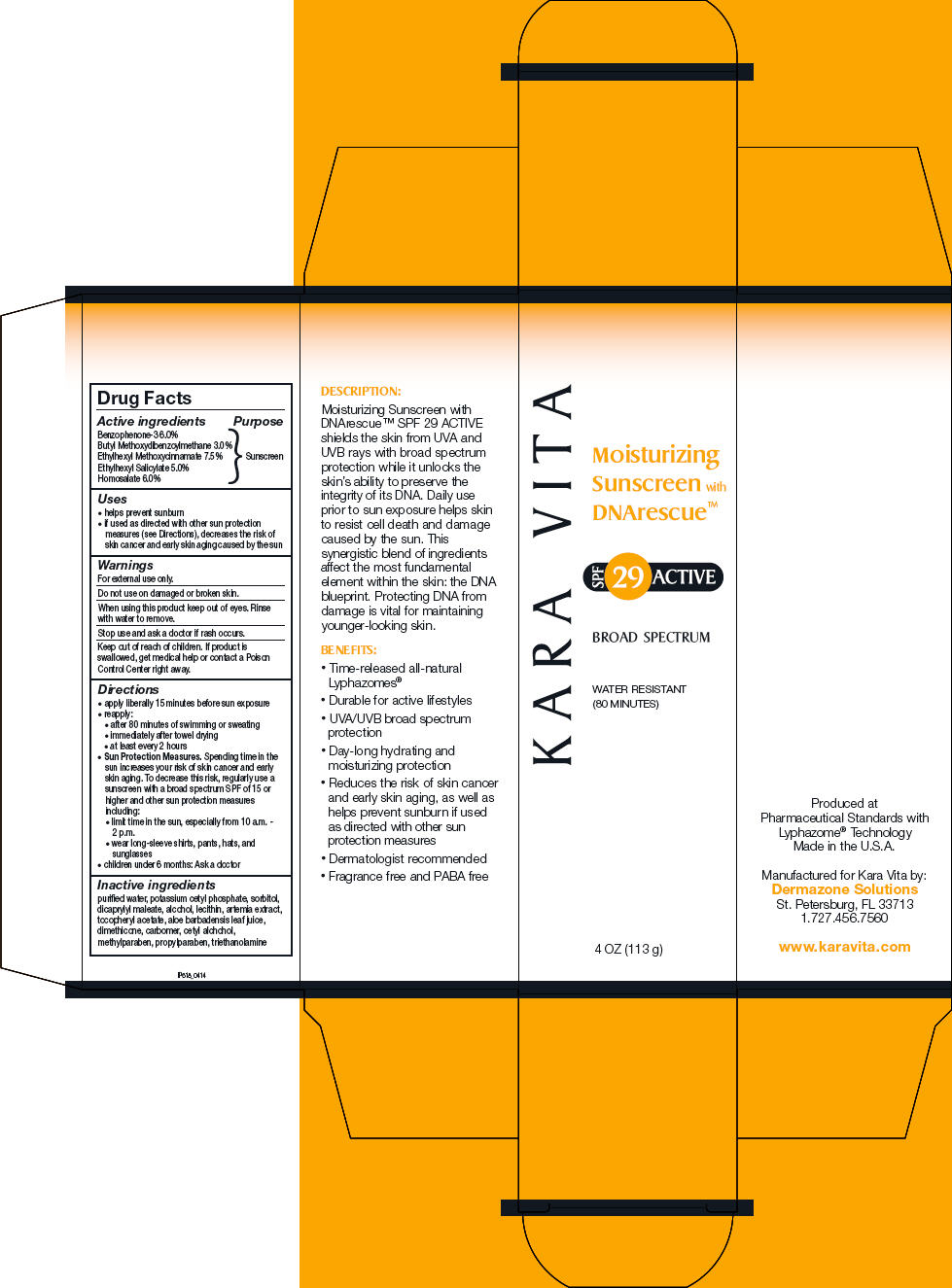 DRUG LABEL: KARA VITA
NDC: 68572-6018 | Form: CREAM
Manufacturer: Kara Vita, Inc.
Category: otc | Type: HUMAN OTC DRUG LABEL
Date: 20250725

ACTIVE INGREDIENTS: OXYBENZONE 60 mg/1 g; AVOBENZONE 30 mg/1 g; OCTINOXATE 75 mg/1 g; OCTISALATE 50 mg/1 g; HOMOSALATE 60 mg/1 g
INACTIVE INGREDIENTS: WATER; POTASSIUM CETYL PHOSPHATE; SORBITOL; DIOCTYL MALEATE; ALCOHOL; .ALPHA.-TOCOPHEROL ACETATE; ALOE VERA LEAF; DIMETHICONE, UNSPECIFIED; CETYL ALCOHOL; METHYLPARABEN; PROPYLPARABEN; TROLAMINE

Karavita
Moisturizing SPF 29 Active with DNArescue™

Drug Facts

Active ingredients

Benzophenone-3 6.0%
Butyl Methoxydibenzoylmethane 3.0%
Ethylhexyl Methoxycinnamate 7.5%
Ethylhexyl Salicylate 5.0%
Homosalate 6.0%

Purpose

Sunscreen

Uses

- helps prevent sunburn
- if used as directed with other sun protection measures (see Directions), decreases the risk of skin cancer and early skin aging caused by the sun

Warnings

For external use only.

Do not use on damaged or broken skin.

When using this product keep out of eyes. Rinse with water to remove.

Stop use and ask a doctor if rash occurs.

Keep out of reach of children. If product is swallowed, get medical help or contact a Poison Control Center right away.

Directions

- apply liberally 15 minutes before sun exposure
- reapply:
  - after 80 minutes of swimming or sweating
  - immediately after towel drying
  - at least every 2 hours
- Sun Protection Measures. Spending time in the sun increases your risk of skin cancer and early skin aging. To decrease this risk, regularly use a sunscreen with a broad spectrum SPF of 15 or higher and other sun protection measures including:
  - limit time in the sun, especially from 10 a.m. - 2 p.m.
  - wear long-sleeve shirts, pants, hats, and sunglasses
- children under 6 months: Ask a doctor

Inactive ingredients

purified water, potassium cetyl phosphate, sorbitol, dicaprylyl maleate, alcohol, lecithin, artemia extract, tocopheryl acetate, aloe barbadensis leaf juice, dimethicone, carbomer, cetyl alchohol, methylparaben, propylparaben, triethanolamine

Manufactured for Kara Vita by:
Dermazone Solutions
St. Petersburg, FL 33713
1.727.456.7560

PRINCIPAL DISPLAY PANEL - 113 g Bottle Carton

KARA VITA

Moisturizing
Sunscreen with
DNArescue™

SPF
29 ACTIVE

BROAD SPECTRUM

WATER RESISTANT
(80 MINUTES)

4 OZ (113 g)